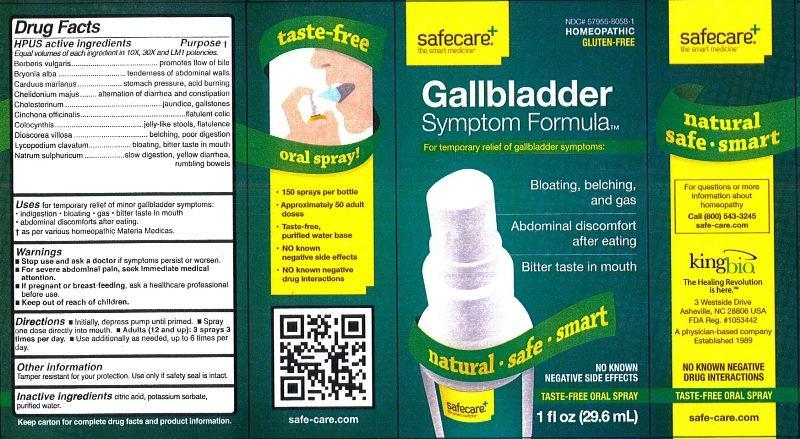 DRUG LABEL: Gallbladder Symptom Formula
NDC: 57955-8058 | Form: LIQUID
Manufacturer: King Bio Inc.
Category: homeopathic | Type: HUMAN OTC DRUG LABEL
Date: 20130220

ACTIVE INGREDIENTS: BERBERIS VULGARIS ROOT BARK 10 [hp_X]/29.6 mL; BRYONIA ALBA ROOT 10 [hp_X]/29.6 mL; SILYBUM MARIANUM SEED 10 [hp_X]/29.6 mL; CHELIDONIUM MAJUS 10 [hp_X]/29.6 mL; CHOLESTEROL 10 [hp_X]/29.6 mL; CINCHONA OFFICINALIS BARK 10 [hp_X]/29.6 mL; CITRULLUS COLOCYNTHIS FRUIT PULP 10 [hp_X]/29.6 mL; DIOSCOREA VILLOSA TUBER 10 [hp_X]/29.6 mL; LYCOPODIUM CLAVATUM SPORE 10 [hp_X]/29.6 mL; SODIUM SULFATE 10 [hp_X]/29.6 mL
INACTIVE INGREDIENTS: CITRIC ACID MONOHYDRATE; POTASSIUM SORBATE; WATER

Gallbladder Symptom Formula

Active Ingredients

HPUS active Ingredients

Equal volumes of each ingredient in 10X, 30X and LM1 potencies.

Berberis vulgaris, Bryonia alba, Carduus marianus, Chelidonium majus, Cholesterinum, Cinchona officinalis, Colocynthis, Dioscorea villosa, Lycopodium clavatum and Natrum sulphuricum.

Inactive Ingredients

Citric acid, potassium sorbate, purified water.

Purpose

HPUS active ingredients

Equal volumes of each ingredient in 10X, 30X and LM1 potencies.

Berberis vulgaris..........................................promotes flow of bile

Bryonia alba.................................................tenderness of abdominal walls

Carduus marianus.......................................stomach pressure, acid burning

Chelidonium majus......................................alternation of diarrhea and constipation

Cholesterinum.............................................jaundice, gallstones

Cinchona officinalis......................................flatulent colic

Colocynthis..................................................jelly-like stools, flatulence

Dioscorea villosa..........................................belching, poor digestion

Lycopodium clavatum...................................bloating, bitter taste in mouth

Natrum sulphuricum.....................................slow digestion, yellow diarrhea, rumbling bowels

Indications and Usage

Uses for temporary relief of minor gallbladder symptoms:

- indigestion
- bloating
- gas
- bitter taste in mouth
- abdominal discomforts after eating

† as per various homeopathic Materia Medicas.

Warnings

- Stop use and ask a doctor if symptoms persist or worsen.
- For severe abdominal pain, seek immediate medical attention.
- If pregnant or breast-feeding, ask a healthcare professional before use.
- Keep out of reach of children.

Other Information

Tamper resistant for your protection. Use only if safety seal is intact.

Keep out of reach of children

Dosage and Administration

Directions:

- Initially, depress pump until primed.
- Spray one dose directly into mouth.
- Adults (12 and up): 3 sprays 3 times per day.
- Use additionally as needed, up to 6 times per day.

PACKAGE LABEL

King Bio Inc.

3 Westside Drive

Asheville, NC 28806

For questions or more information about homeopathy call (800) 543-3245 or safe-care.com